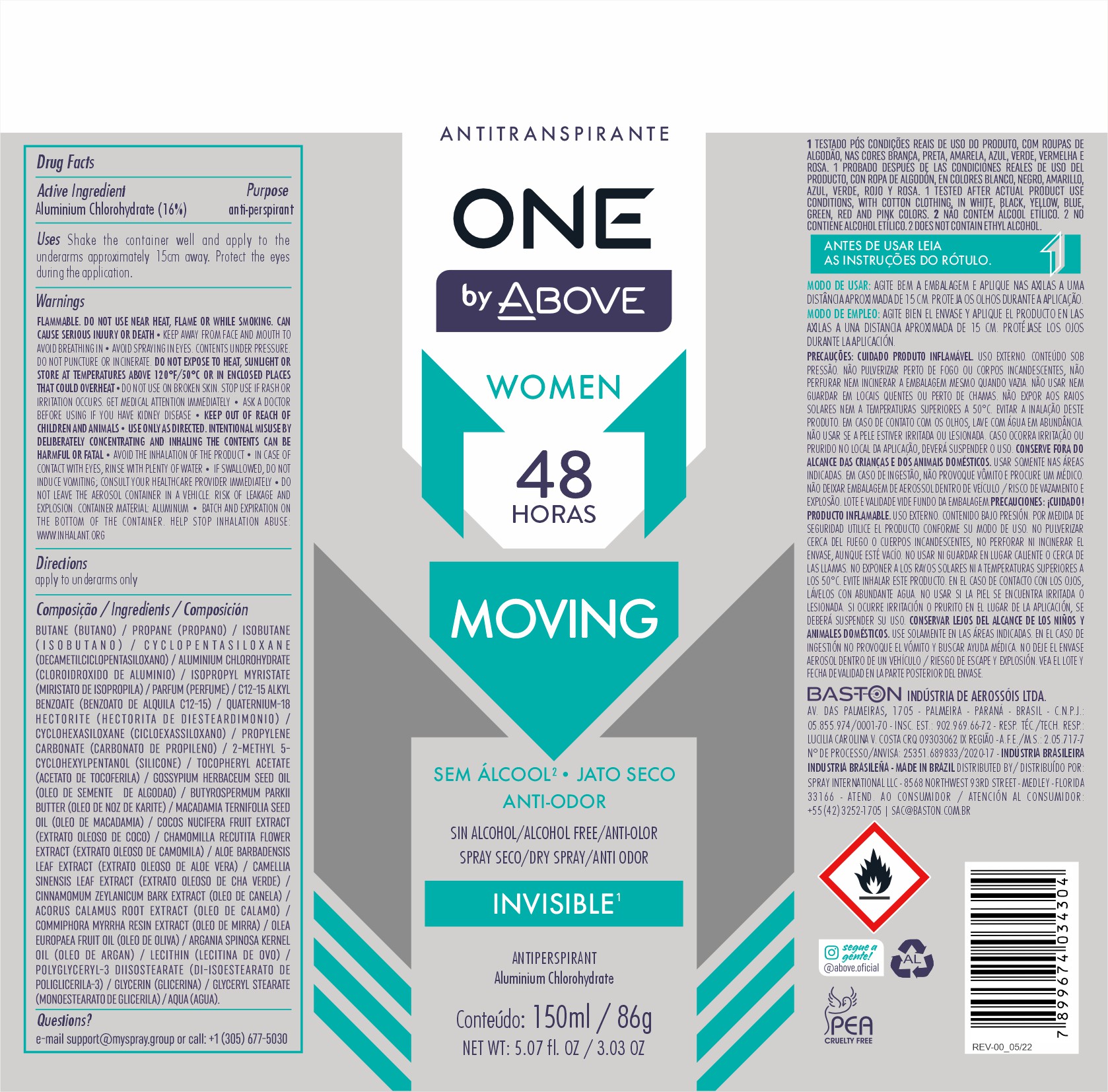 DRUG LABEL: ANTIPERSPIRANT ABOVE ONE BY MOVING WOMEN
NDC: 73306-1151 | Form: AEROSOL, SPRAY
Manufacturer: BASTON INDUSTRIA DE AEROSSOIS LTDA
Category: otc | Type: HUMAN OTC DRUG LABEL
Date: 20240423

ACTIVE INGREDIENTS: ALUMINUM CHLOROHYDRATE 16 g/100 g
INACTIVE INGREDIENTS: ISOBUTANE

ANTIPERSPIRANT ABOVE ONE BY MOVING WOMEN

ACTIVE INGREDIENT

Aluminium Chlorohydrate

PURPOSE

UNDERARM ANTIPERSPIRANT DEODORANT

INDICATIONS AND USAGE

Shake the container well and apply to the underarms approximately 15cm away. Protect the eyes during the application.

INACTIVE INGREDIENT

BUTANE (BUTANO) / PROPANE (PROPANO) / ISOBUTANE (ISOBUTANO) / CYCLOPENTASILOXANE (DECAMETILCICLOPENTASILOXANO) / ALUMINIUM CHLOROHYDRATE (CLOROIDROXIDO DE ALUMINIO) / ISOPROPYL MYRISTATE (MIRISTATO DE ISOPROPILA) / PARFUM

WARNINGS AND PRECAUTIONS

FLAMMABLE. DO NOT USE NEAR HEAT, FLAME OR WHILE SMOKING. CAN CAUSE SERIOUS INJURY OR DEATH KEEP AWAY FROM FACE AND MOUTH TO AVOID BREATHING IN AVOID SPRAYING IN EYES. CONTENTS UNDER PRESSURE. DO NOT PUNCTURE OR INCINERATE. DO NOT

WARNINGS

FLAMMABLE. DO NOT USE NEAR HEAT, FLAME OR WHILE SMOKING. CAN CAUSE SERIOUS INJURY OR DEATH KEEP AWAY FROM FACE AND MOUTH TO AVOID BREATHING IN AVOID SPRAYING IN EYES. CONTENTS UNDER PRESSURE. DO NOT PUNCTURE OR INCINERATE. DO NOT

QUESTIONS

MAIL : SUPPORT@MYSPRAY.GROUP OR CALL (305) 677-5030

KEEP OUT OF REACH OF CHILDREN

DOSAGE AND ADMINISTRATION

make use of it whenever you find it necessary